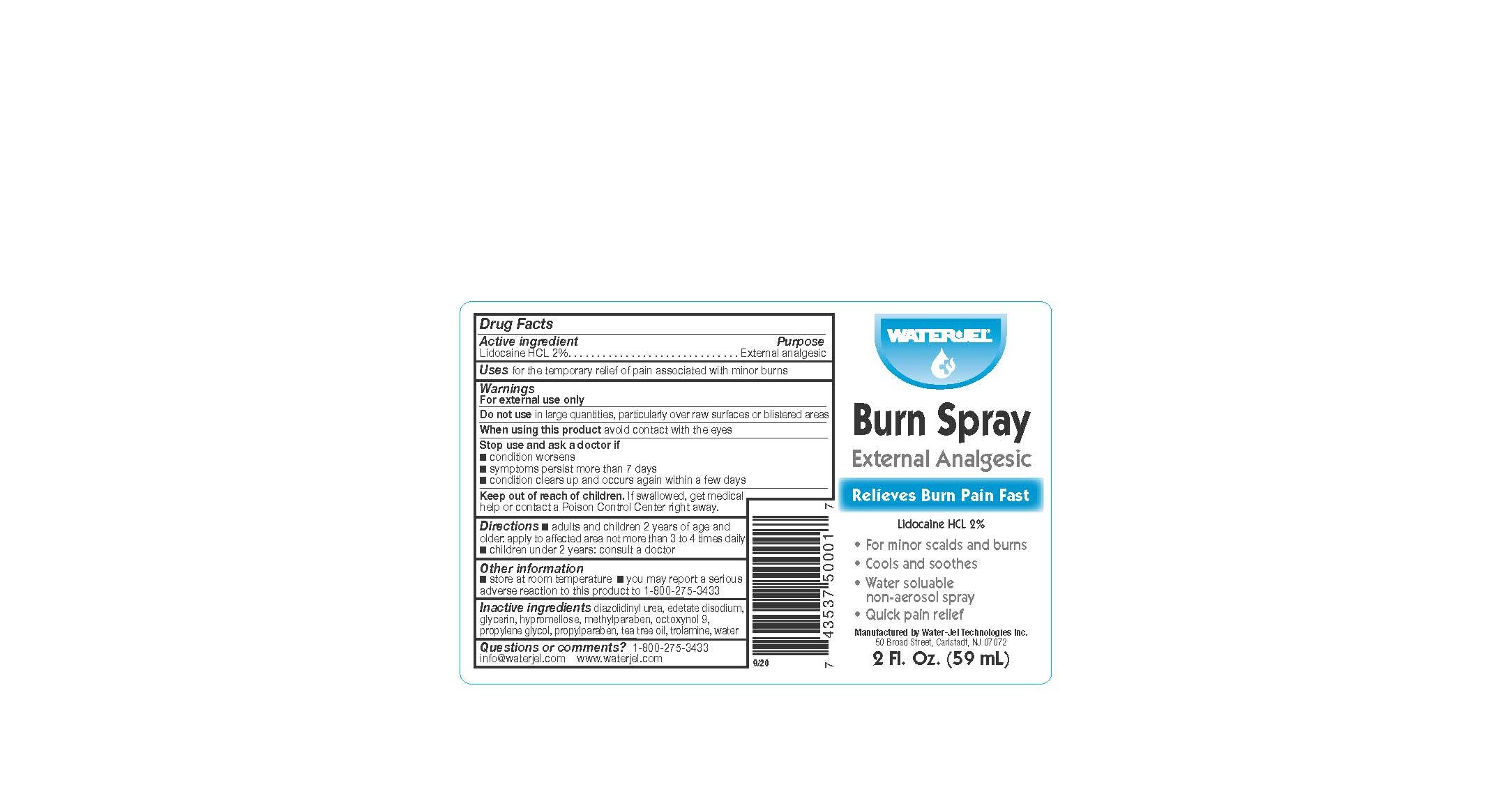 DRUG LABEL: Burn Mist
NDC: 59898-201 | Form: SPRAY
Manufacturer: Water-Jel Technologies
Category: otc | Type: HUMAN OTC DRUG LABEL
Date: 20250107

ACTIVE INGREDIENTS: LIDOCAINE HYDROCHLORIDE 2 g/100 mL
INACTIVE INGREDIENTS: EDETATE DISODIUM; OCTOXYNOL 9; GLYCERIN; HYPROMELLOSE 2208 (100000 MPA.S); TROLAMINE; TEA TREE OIL; PROPYLPARABEN; METHYLPARABEN; PROPYLENE GLYCOL; DIAZOLIDINYL UREA; WATER

Burn Spray

Active ingredient

Lidocaine HCl 2%

Purpose

External analgesic

Uses

for the temporary relief of pain associated with minor burns

Warnings

For external use only

Do not use

in large quantities, particularly over raw surfaces or blistered areas

When using this product

avoid contact with eyes

STOP USE

- condition worsens
- symptoms persist for more than 7 days
- condition clears up and occurs again within a few days

Keep out of the reach of children

If swallowed, get medical help or contact a Poison Control Center right away.

DOSAGE AND ADMINISTRATION

- adults and children 2 years of age and older: apply to affected area not more than 3 to 4 times daily
- children under 2 years of age: consult a doctor

Other information

store at room temperature

you may report a serious adverse reaction to this product to 1-800-275-3433

Inactive ingredients

diazolidinyl urea, edetate disodium, glycerin, hypromellose, methylparaben, octoxynol 9, propylene glycol, propylparaben, tea tree oil, trolamine, water

Questions or comments?

1-800-275-3433 info@waterjel.com www.waterjel.com
Manufactered by Water-Jel Technologies, Inc., 50 Broad Street,
Carlstadt, NJ 07072, USA